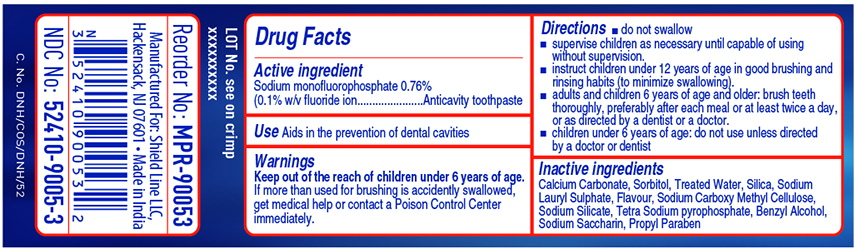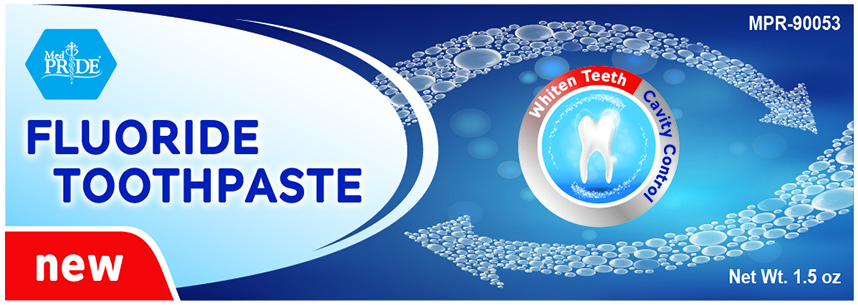 DRUG LABEL: Medpride
NDC: 52410-9005 | Form: PASTE, DENTIFRICE
Manufacturer: Shield Line LLC
Category: otc | Type: HUMAN OTC DRUG LABEL
Date: 20250116

ACTIVE INGREDIENTS: SODIUM MONOFLUOROPHOSPHATE 7.6 mg/1 g
INACTIVE INGREDIENTS: CALCIUM CARBONATE; WATER; SORBITOL; HYDRATED SILICA; SODIUM LAURYL SULFATE; CARBOXYMETHYLCELLULOSE SODIUM; SACCHARIN SODIUM; METHYLPARABEN SODIUM; PROPYLPARABEN

Drug Facts

Active Ingredient

Sodium monofluorophosphate 0.76% (0.1% w/v fluoride ion)

Purpose

Anticavity toothpaste

Uses

aids in the prevention of dental cavities

Warning

Keep out of the reach of children under 6 years of age

WARNINGS

If more than used for brushing is accidently swallowed, get medical help or contact a Poison Control Center immediately

Directions

■ do not swallow ■ supervise children as necessary until capable of using without supervision ■ instruct children under 12 years of age in good brushing and rinsing habits (to minimize swallowing) ■ adults and children 6 years of age and older: brush teeth thoroughly, preferably after each meal or at least twice a day, or as directed by a dentist or doctor ■ children under 6 years of age: do not use unless directed by a doctor or dentist

Inactive ingredients

calcium carbonate, water, sorbitol, hydrated silica, sodium lauryl sulfate, sodium carboxymethyl cellulose, sodium saccharin, sodium methylparaben, sodium propylparaben